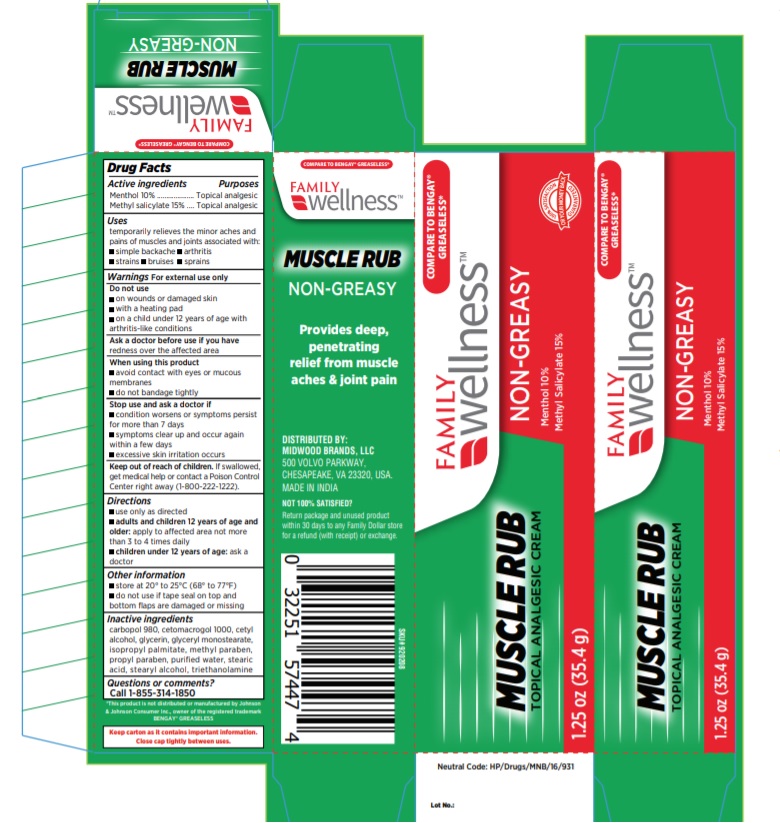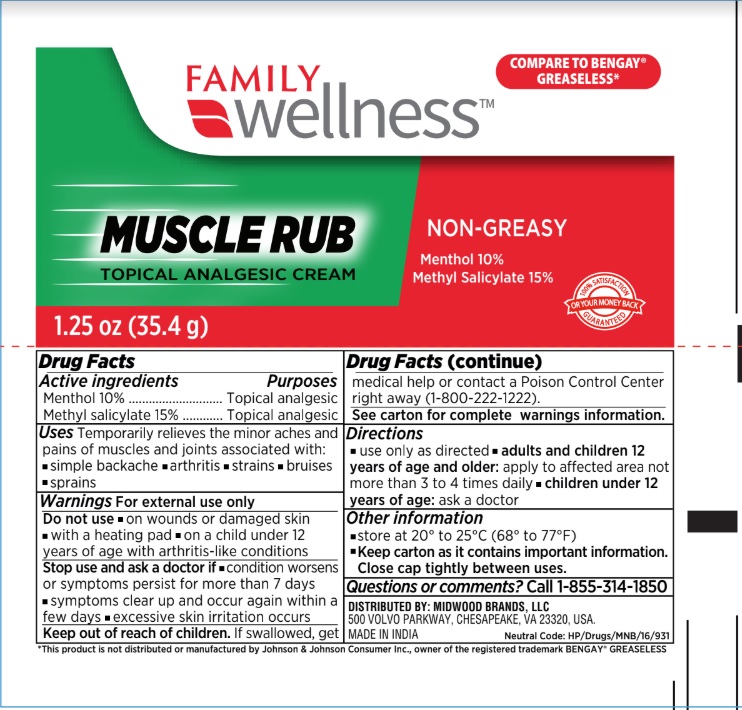 DRUG LABEL: Family Wellness Pain Relieving
NDC: 76168-606 | Form: CREAM
Manufacturer: Velocity Pharma LLC
Category: otc | Type: HUMAN OTC DRUG LABEL
Date: 20200702

ACTIVE INGREDIENTS: MENTHOL, UNSPECIFIED FORM 100 mg/1 g; METHYL SALICYLATE 150 mg/1 g
INACTIVE INGREDIENTS: CETYL ALCOHOL; GLYCERIN; GLYCERYL MONOSTEARATE; ISOPROPYL PALMITATE; METHYLPARABEN; PHENOXYETHANOL; POTASSIUM CETYL PHOSPHATE; POTASSIUM HYDROXIDE; PROPYLPARABEN; STEARIC ACID; WATER; XANTHAN GUM; CETETH-20; TROLAMINE

Family Wellness Muscle Rub, Pain-relieving cream

Drug Facts

Active ingredients............. Purpose
Menthol 10%..................... Topical analgesic
Methyl salicylate 15%......... Topical analgesic

Active ingredients | Purpose
Menthol 10% | Topical analgesic
Methyl salicylate 15% | Topical analgesic

Uses

temporarily relieves the minor aches and pains of muscles and joints associated with:

- simple backache
- arthritis
- strains
- bruises
- sprains

Warnings

For external use only.

Do not use

- on wounds or damaged skin
- with a heating pad
- on a child under 12 years of age with arthritis-like conditions

Ask a doctor before use if you have redness over the affected area.

When using this product

- avoid contact with eyes or mucous membranes
- do not bandage tightly

Stop use and ask a doctor if

- condition worsens or symptoms persist for more than 7 days
- symptoms clear up and occur again within a few days
- excessive skin irritation occurs

Keep out of reach of children to avoid accidental ingestion. If swallowed, get medical help or contact a Poison Control Center immediately.

Directions

- use only as directed
- adults and children 12 years of age and older: apply to affected area not more than 3 to 4 times daily
- children under 12 years of age: ask a doctor

Other information

- store at 20° to 25°C (68° to 77°F)

Inactive ingredients

cetyl alcohol, glycerin, glyceryl stearate, isopropyl palmitate, methylparaben, phenoxyethanol, potassium cetyl phosphate, potassium hydroxide, propylparaben, stearic acid, water, xanthan gum